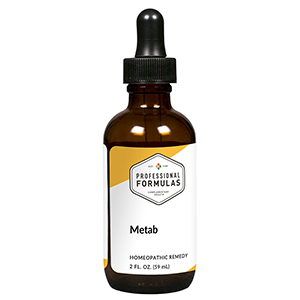 DRUG LABEL: Metab
NDC: 63083-6012 | Form: LIQUID
Manufacturer: Professional Complementary Health Formulas
Category: homeopathic | Type: HUMAN OTC DRUG LABEL
Date: 20190815

ACTIVE INGREDIENTS: THYROID, UNSPECIFIED 6 [hp_X]/59 mL; SODIUM CHLORIDE 6 [hp_X]/59 mL; ANHYDROUS CITRIC ACID 12 [hp_X]/59 mL; GLUTAMINE 10 [hp_X]/59 mL; UBIDECARENONE 12 [hp_X]/59 mL
INACTIVE INGREDIENTS: ALCOHOL; WATER

X12

ACTIVE INGREDIENTS

2 FL. OZ. contains
Glandular tissue mix 6X (12.3 mL), 30X (12.3 mL)
Cell salt mix 6X (9.8 mL), 12X (9.8 mL)
Krebs cycle constituents 12X (4.9 mL), 30X (4.9 mL)
Amino acid mix 10X (1 mL), 30X (1 mL)
Coenzyme Q10 12X (1 mL)
RNA-DNA 30X (1 mL), 100X (1 mL)

QUESTIONS

Professional Formulas

PO Box 2034 Lake Oswego, OR 97035

INDICATIONS

For the temporary relief of difficulty maintaining proper weight, poor appetite, minor abdominal pain, bloating, increased urination, fatigue, or lethargy.*

PURPOSE

*Claims based on traditional homeopathic practice, not accepted medical evidence. Not FDA evaluated.

WARNINGS

Consult a doctor if condition worsens or symptoms persist. Keep out of the reach of children. In case of overdose, get medical help or contact a poison control center right away. If pregnant or breastfeeding, ask a healthcare professional before use.

Keep out of the reach of children.

PREGNANCY OR BREAST FEEDING

If pregnant or breastfeeding, ask a healthcare professional before use.

DIRECTIONS

Place drops under tongue 30 minutes before/after meals. Adults and children 12 years and over: Take 10 drops up to 3 times per day. Consult a physician for use in children under 12 years of age.

OTHER INFORMATION

Tamper resistant. If seal is broken, do not use. After opening, close container tightly and store at room temperature away from heat.

INACTIVE INGREDIENTS

20% ethanol, purified water.

LABEL

Est 1985

Professional Formulas

Complementary Health

Metab

Homeopathic Remedy

2 FL. OZ. (59 mL)